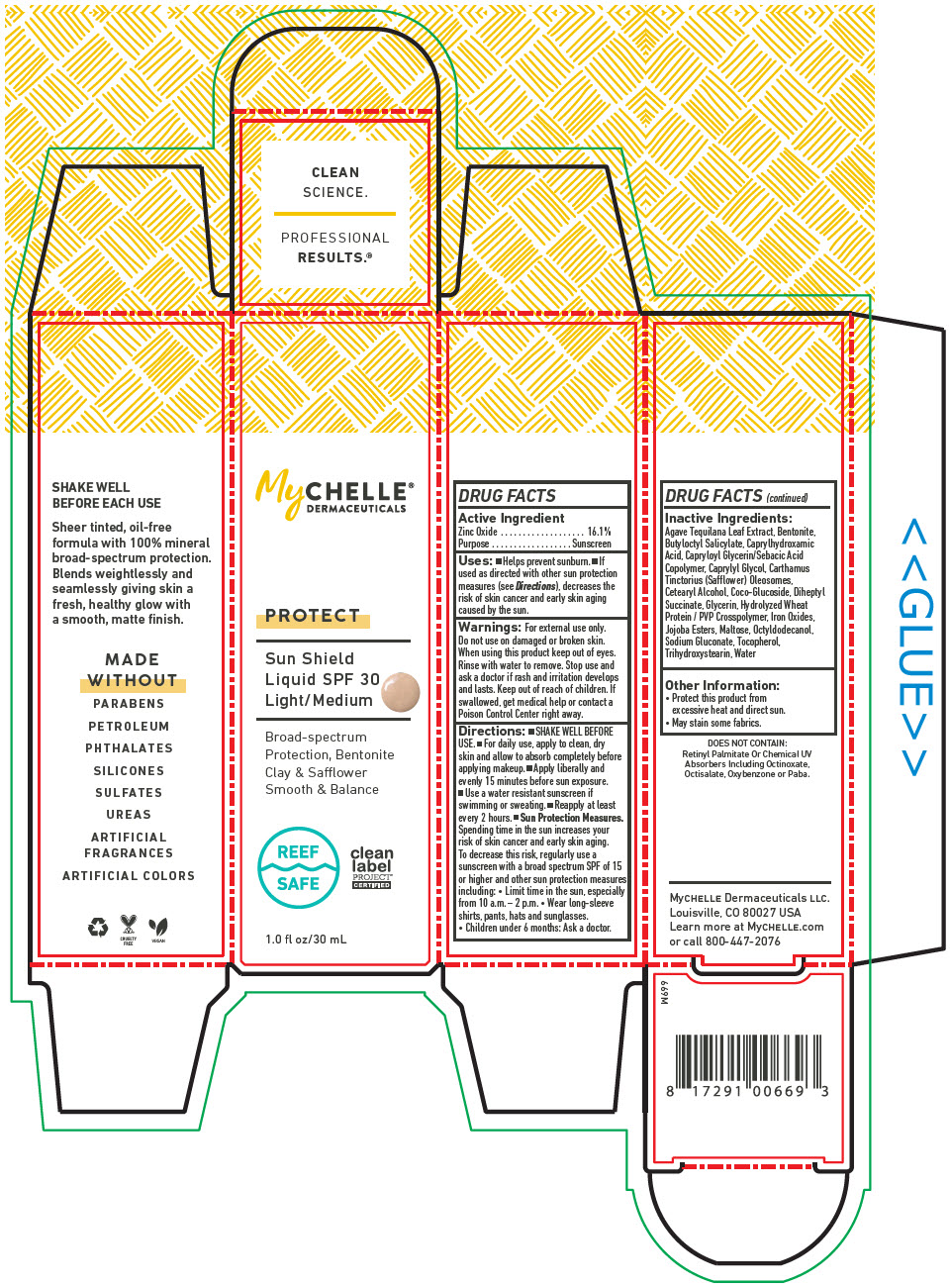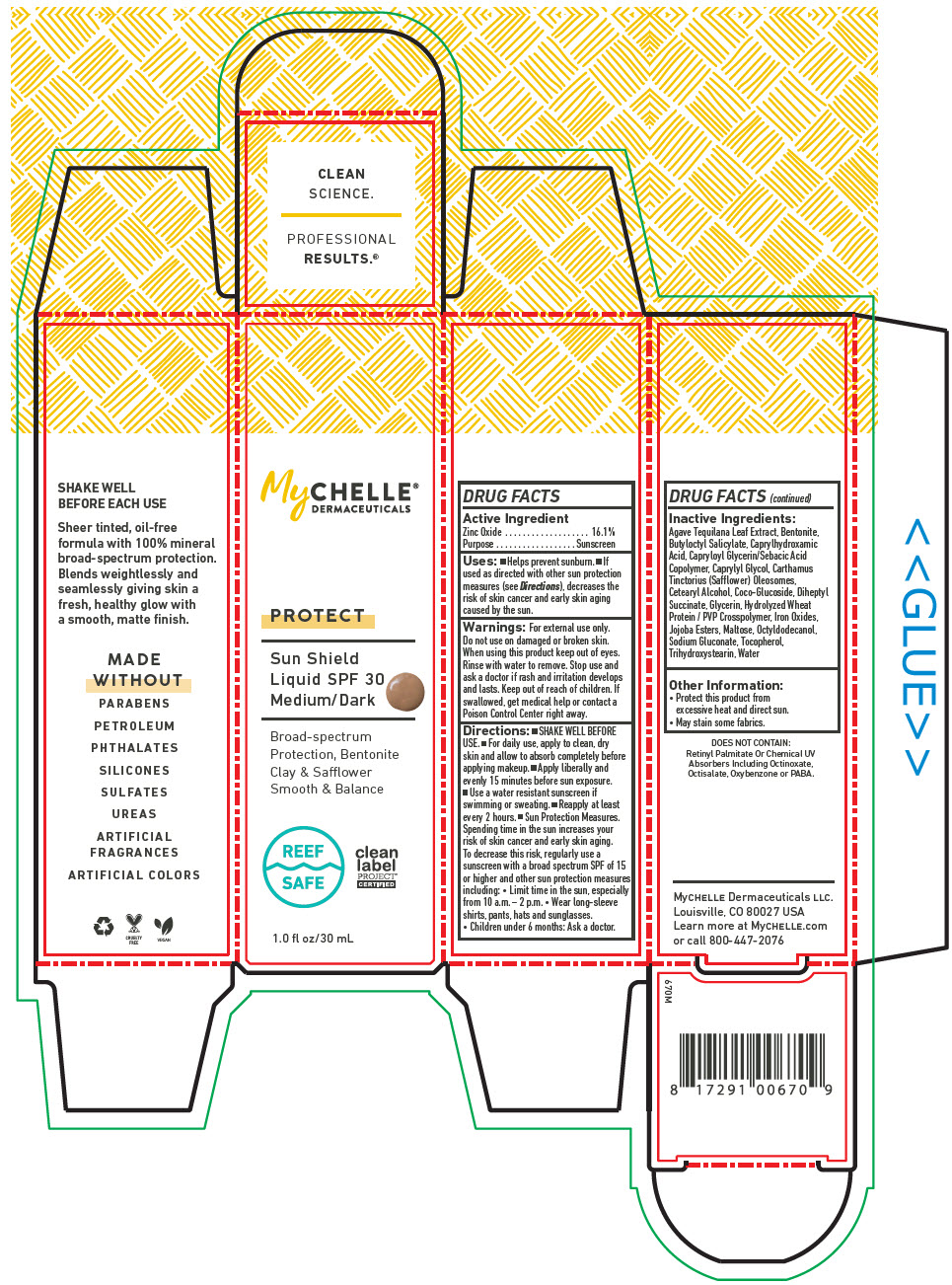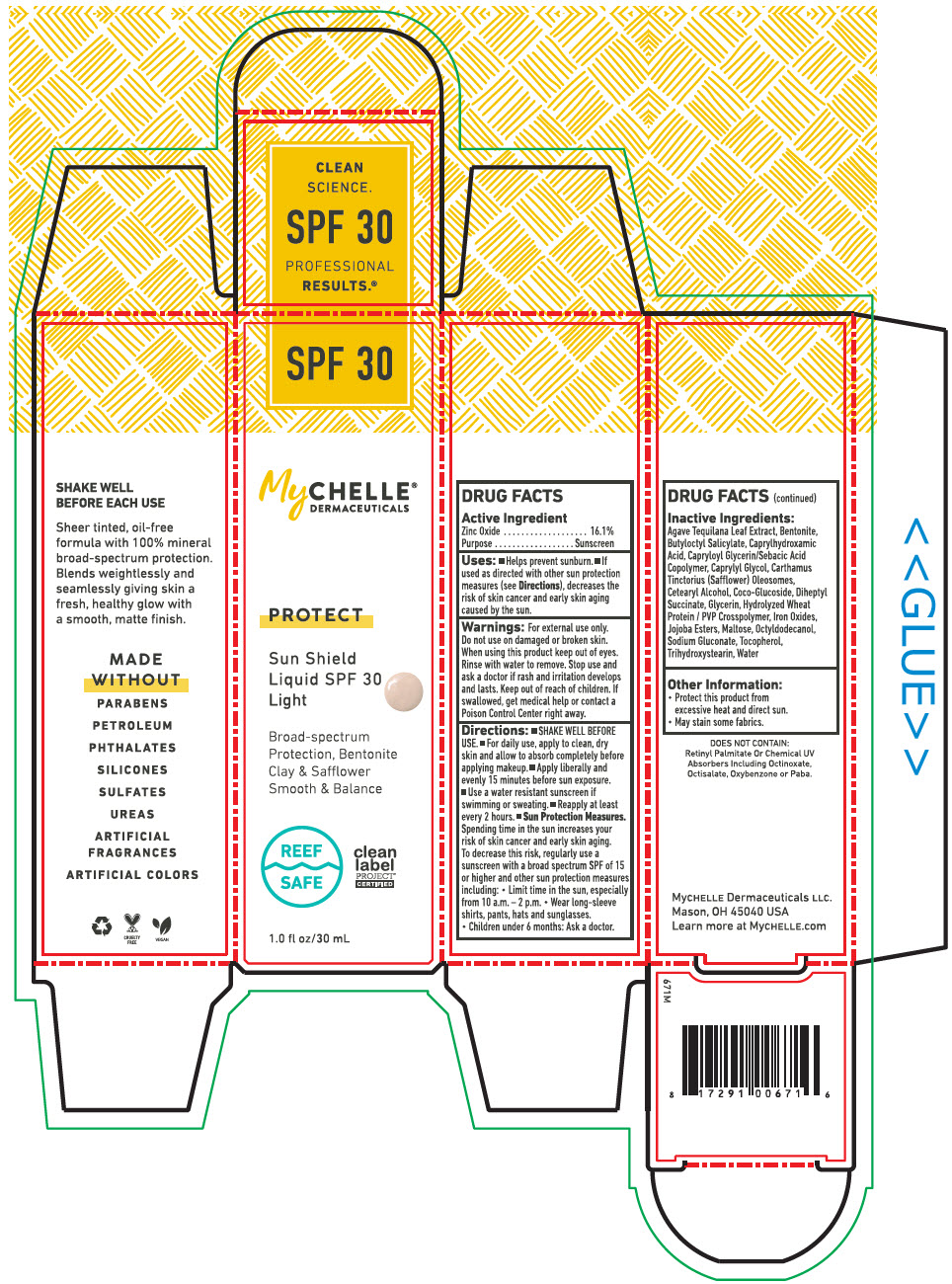 DRUG LABEL: MyChelle Dermaceuticals Sun Shield SPF 30 Light/Medium 
NDC: 72805-669 | Form: LIQUID
Manufacturer: French Transit, Ltd.
Category: otc | Type: HUMAN OTC DRUG LABEL
Date: 20221215

ACTIVE INGREDIENTS: Zinc Oxide 16.1 g/100 mL
INACTIVE INGREDIENTS: Water; Agave Tequilana Leaf; Bentonite; Butyloctyl Salicylate; Caprylhydroxamic Acid; Capryloyl Glycerin/Sebacic Acid Copolymer (2000 MPA.S); Caprylyl Glycol; Carthamus Tinctorius Seed Oleosomes; Cetostearyl Alcohol; Coco Glucoside; Diheptyl Succinate; Glycerin; Hydrolyzed Wheat Protein (Enzymatic; 3000 MW); Ferric Oxide Red; HYDROGENATED JOJOBA OIL, RANDOMIZED; MALTOSE, UNSPECIFIED FORM; Octyldodecanol; Sodium Gluconate; Tocopherol; Trihydroxystearin

MyChelle® Dermaceuticals Sun Shield SPF 30
Protect

DRUG FACTS

Active Ingredient

Zinc Oxide 16.1%

Purpose

Sunscreen

Uses

- Helps prevent sunburn.
- If used as directed with other sun protection measures (see Directions), decreases the risk of skin cancer and early skin aging caused by the sun.

Warnings

For external use only. Do not use on damaged or broken skin. When using this product keep out of eyes. Rinse with water to remove. Stop use and ask a doctor if rash and irritation develops and lasts.

Keep out of reach of children. If swallowed, get medical help or contact a Poison Control Center right away.

Directions

- SHAKE WELL BEFORE USE.
- For daily use, apply to clean, dry skin and allow to absorb completely before applying makeup.
- Apply liberally and evenly 15 minutes before sun exposure.
- Use a water resistant sunscreen if swimming or sweating.
- Reapply at least every 2 hours.
- Sun Protection Measures. Spending time in the sun increases your risk of skin cancer and early skin aging. To decrease this risk, regularly use a sunscreen with a broad spectrum SPF of 15 or higher and other sun protection measures including:
  - Limit time in the sun, especially from 10 a.m. – 2 p.m.
  - Wear long-sleeve shirts, pants, hats and sunglasses.
  - Children under 6 months: Ask a doctor.

Inactive Ingredients

Agave Tequilana Leaf Extract, Bentonite, Butyloctyl Salicylate, Caprylhydroxamic Acid, Capryloyl Glycerin/Sebacic Acid Copolymer, Caprylyl Glycol, Carthamus Tinctorius (Safflower) Oleosomes, Cetearyl Alcohol, Coco-Glucoside, Diheptyl Succinate, Glycerin, Hydrolyzed Wheat Protein / PVP Crosspolymer, Iron Oxides, Jojoba Esters, Maltose, Octyldodecanol, Sodium Gluconate, Tocopherol, Trihydroxystearin, Water

Other Information

- Protect this product from excessive heat and direct sun.
- May stain some fabrics.

PRINCIPAL DISPLAY PANEL - 30 mL Bottle Box - Light/Medium

MyCHELLE®
DERMACEUTICALS

PROTECT

Sun Shield
Liquid SPF 30
Light/Medium

Broad-spectrum
Protection, Bentonite
Clay & Safflower
Smooth & Balance

REEF
SAFE

clean
label
PROJECT®
CERTIFIED

1.0 fl oz/30 mL

PRINCIPAL DISPLAY PANEL - 30 mL Bottle Box - Medium/Dark

MyCHELLE®
DERMACEUTICALS

PROTECT

Sun Shield
Liquid SPF 30
Medium/Dark

Broad-spectrum
Protection, Bentonite
Clay & Safflower
Smooth & Balance

REEF
SAFE

clean
label
PROJECT®
CERTIFIED

1.0 fl oz/30 mL

PRINCIPAL DISPLAY PANEL - 30 mL Bottle Box - Light

SPF 30

MyCHELLE®
DERMACEUTICALS

PROTECT

Sun Shield
Liquid SPF 30
Light

Broad-spectrum
Protection, Bentonite
Clay & Safflower
Smooth & Balance

REEF
SAFE

clean
label
PROJECT®
CERTIFIED

1.0 fl oz/30 mL